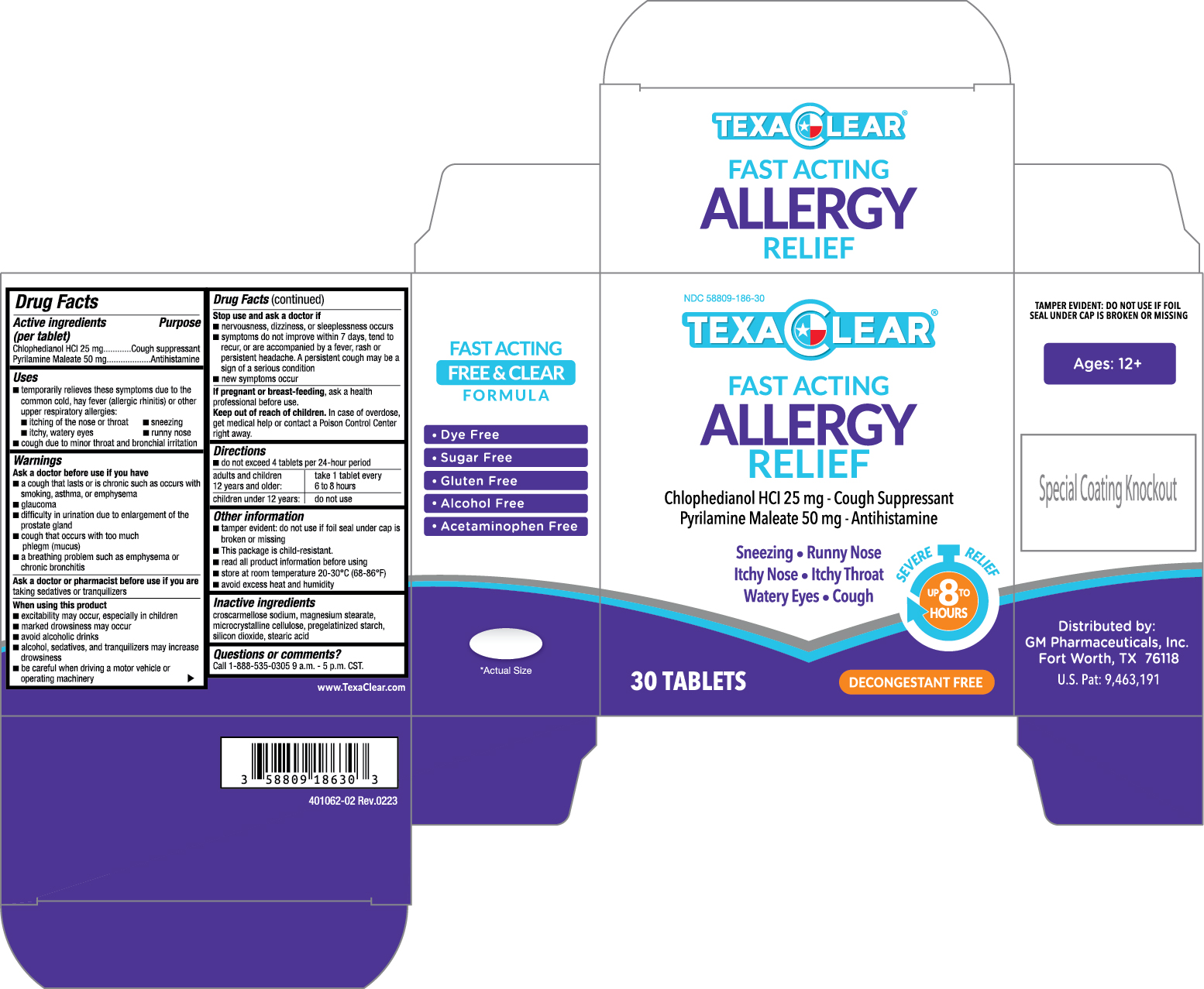 DRUG LABEL: TexaClear
NDC: 58809-186 | Form: TABLET
Manufacturer: GM Pharmaceuticals, INC
Category: otc | Type: HUMAN OTC DRUG LABEL
Date: 20241007

ACTIVE INGREDIENTS: CHLOPHEDIANOL HYDROCHLORIDE 25 mg/1 1; PYRILAMINE MALEATE 50 mg/1 1
INACTIVE INGREDIENTS: CROSCARMELLOSE SODIUM; MAGNESIUM STEARATE; CELLULOSE, MICROCRYSTALLINE; SILICON DIOXIDE; STARCH, CORN; STEARIC ACID

TexaClear Fast Acting Allergy Relief Tablet

TEXACLEAR-ALLERGY RELIEF (Chlophedianol HCl, Pyrilamine Maleate) TABLET

GM Pharmaceuticals, Inc.

TexaClear Allergy Relief Tablet 30 count

Drug Facts

Active Ingredients (per tablet)

Chlophedianol HCl ...... 25 mg

Pyrilamine Maleate ...... 50 mg

Purpose

Cough Suppressant

Antihistamine

Uses

- temporarily relieves these symptoms due to the common cold, hay fever (allergic rhinitis) or other upper respiratory allergies:
  - runny nose
  - itchy, watery eyes
  - itching of the nose or throat
  - sneezing
  - cough due to minor throat and bronchial irritation

Warnings

Ask a doctor before use if you have

- a cough that lasts or is chronic such as occurs with smoking, asthma, or emphysema
- a cough that occurs with too much phlegm (mucus)
- glaucoma
- a breathing problem such as emphysema or chronic bronchitis
- difficulty in urination due to enlargement of the prostate gland

Ask a doctor or pharmacist before use if you are

taking sedatives or tranquilizers

When using this product

- excitability may occur, especially in children
- marked drowsiness may occur
- avoid alcoholic drinks
- alcohol, sedatives, and tranquilizers may increase drowsiness
- be careful when driving a motor vehicle or operating machinery

Stop use and ask a doctor if:

- nervousness, dizziness, or sleeplessness occurs
- symptoms do not improve within 7 days, tend to recur, or are accompanied by a fever, rash or persistent headache. A persistent cough may be a sign of a serious condition
- new symptoms occur

If pregnant or breast-feeding,

ask a health professional before use

Keep out of reach of children.

In case of overdose, get medical help or contact a Poison Control Center right away.

Directions

- do not exceed 4 tablets per 24-hour period.

adults and children 12 years and older: | take 1 tablet every 6 to 8 hours.
children under 12 years: | do not use.

Other Information

- tamper evident: do not use if foil seal under the cap is broken or missing
- This package is child-resistant.
- read all information before using
- store at room temperature 20-30°C (68-86°F)
- avoid excess heat and humidity

Inactive Ingredients

croscarmellose sodium, magnesium stearate, microcrystalline cellulose, pregelatinized starch, silicon dioxide, stearic acid

Questions or comments?

Call 1-888-535-0305 9 a.m.-5 p.m. CST

PRINCIPAL DISPLAY PANEL

NDC 58809-186-30

TEXACLEAR

ALLERGY

RELIEF

30 Tablets